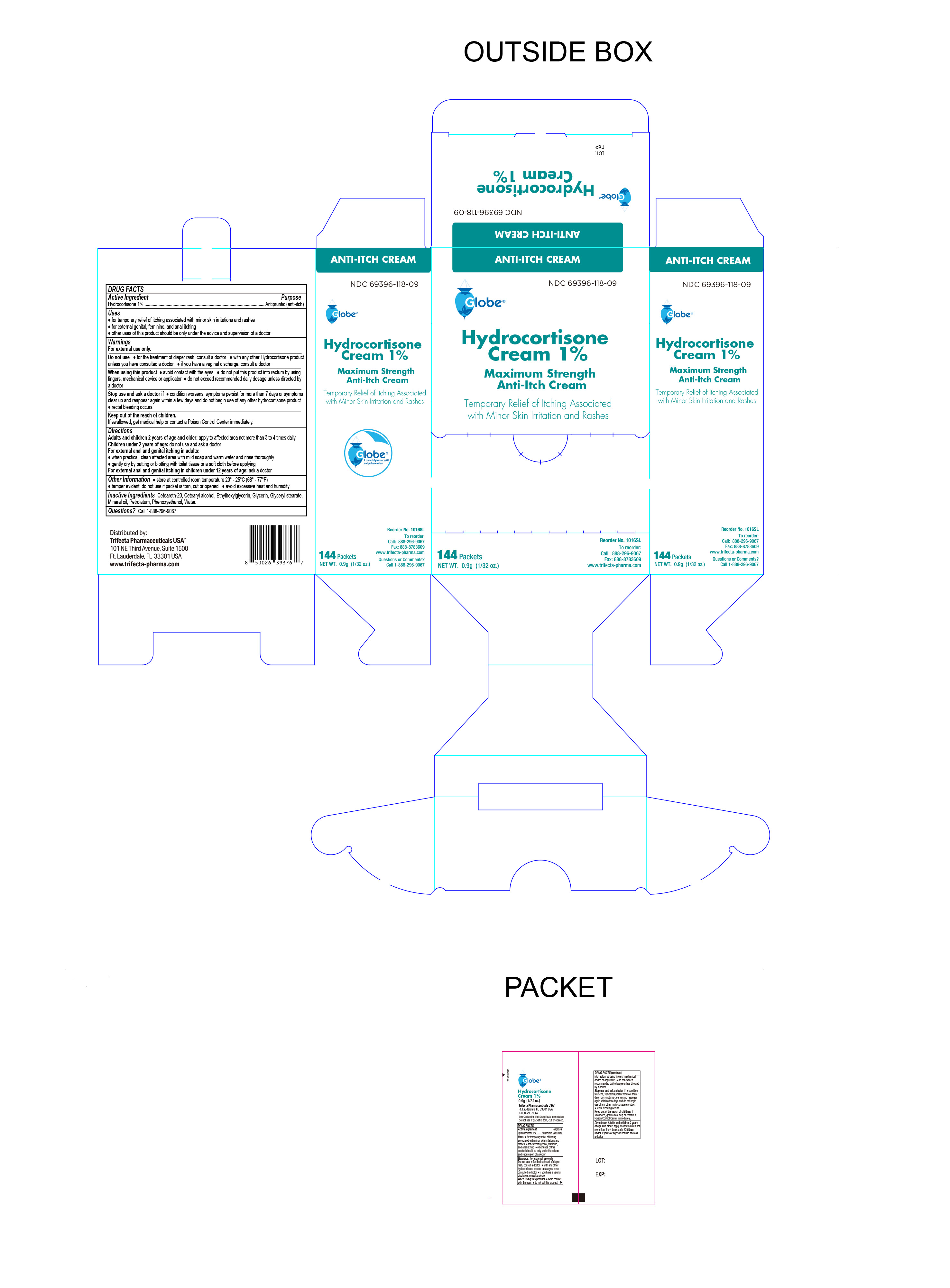 DRUG LABEL: Hydrocortisone 1%
NDC: 69396-118 | Form: CREAM
Manufacturer: Trifecta Pharmaceuticals Usa Llc
Category: otc | Type: HUMAN OTC DRUG LABEL
Date: 20250823

ACTIVE INGREDIENTS: HYDROCORTISONE 1 g/100 g
INACTIVE INGREDIENTS: PHENOXYETHANOL; MINERAL OIL; GLYCERIN; GLYCERYL MONOSTEARATE; PETROLATUM; WATER; POLYOXYL 20 CETOSTEARYL ETHER; CETOSTEARYL ALCOHOL; ETHYLHEXYLGLYCERIN

Globe Hydrocortisone Cream 1%
MAXIMUM STRENGTH

Active ingredient

Hydrocortisone 1%

Purpose

Antipruritic (Anti-Itch)

Keep out of the reach of children.

If swallowed, get medical help or contact a Poison Control Center immediately.

Uses

For temporary relief of itching associated with minor skin irritations and rashes

● external feminine, genital and anal itching

Other uses of this product should be only under the advice and supervision of a doctor

Do Not Use

- For the treatment of diaper rash, consult a doctor.
- With any other Hydrocortisone product unless you have consulted a doctor
- If you have a vaginal discharge, consult a doctor

Warnings

For external use only

When using this product

- Avoid Contact with the eyes
- do not exceed the recommended daily dosage unless directed by a doctor.
- do not put this product into the rectum by using fingers or any mechanical device or applicator.

Stop using this product and ask a doctor if

- conditions worsens, symptoms persist for more than 7 days or symptoms clear up and reappear again within a few days and do not begin use of any other hydrocortisone product.
- Rectal bleeding occurs

Directions

Adults and children 2 years of age and older: apply to the affected area not more than 3 to 4 times daily.

Children under 2 years of age: do not use and ask a doctor.

For External and anal itching in adults:

When practical, clean affected area with mild soap and warm water and rinse thoroughly

Gently dry by patting or blotting with toilet tissue or a soft cloth before applying

For External anal and genital itching in children under 12 years of age:

Ask a doctor

Inactive ingredients

Ceteareth-20, Cetearyl alcohol, Ethylhexylglycerin, Glycerin, Glyceryl Stearate, mineral oil, petrolatum, Phenoxyethanol, water.

Other information

● store at controlled room temperature 20°-25°C (68 °- 77 °F)

Tamper evident, do not use if packet is torn, cut or opened.

Avoid excessive heat and humidity.

Distributed by:

Trifecta Pharmaceuticals USA™

Ft. Lauderdale, FL 33301 USA

Online: www.trifecta-pharma.com

Reorder No. 1016SL

To reorder call: 1-888-296-9067

Fax: 888-878-3609

Questions

Call 1-888-296-9067